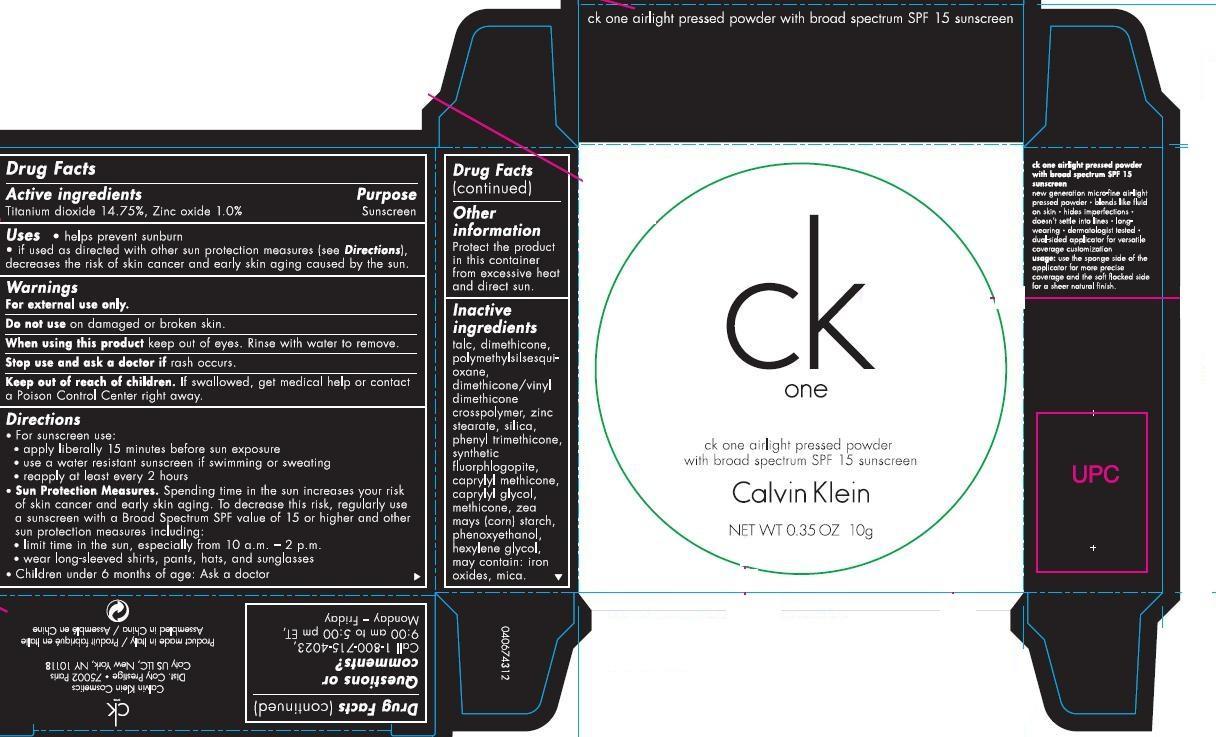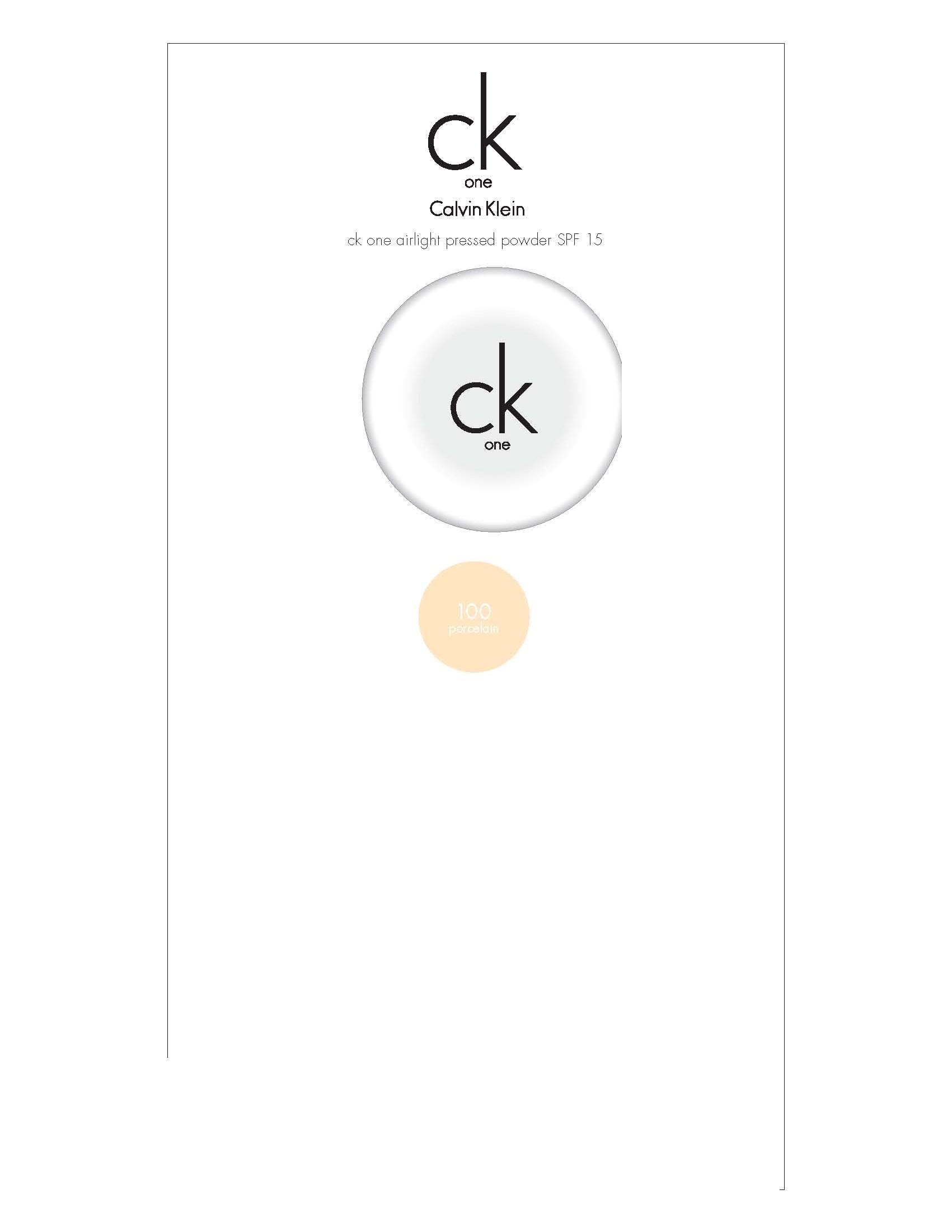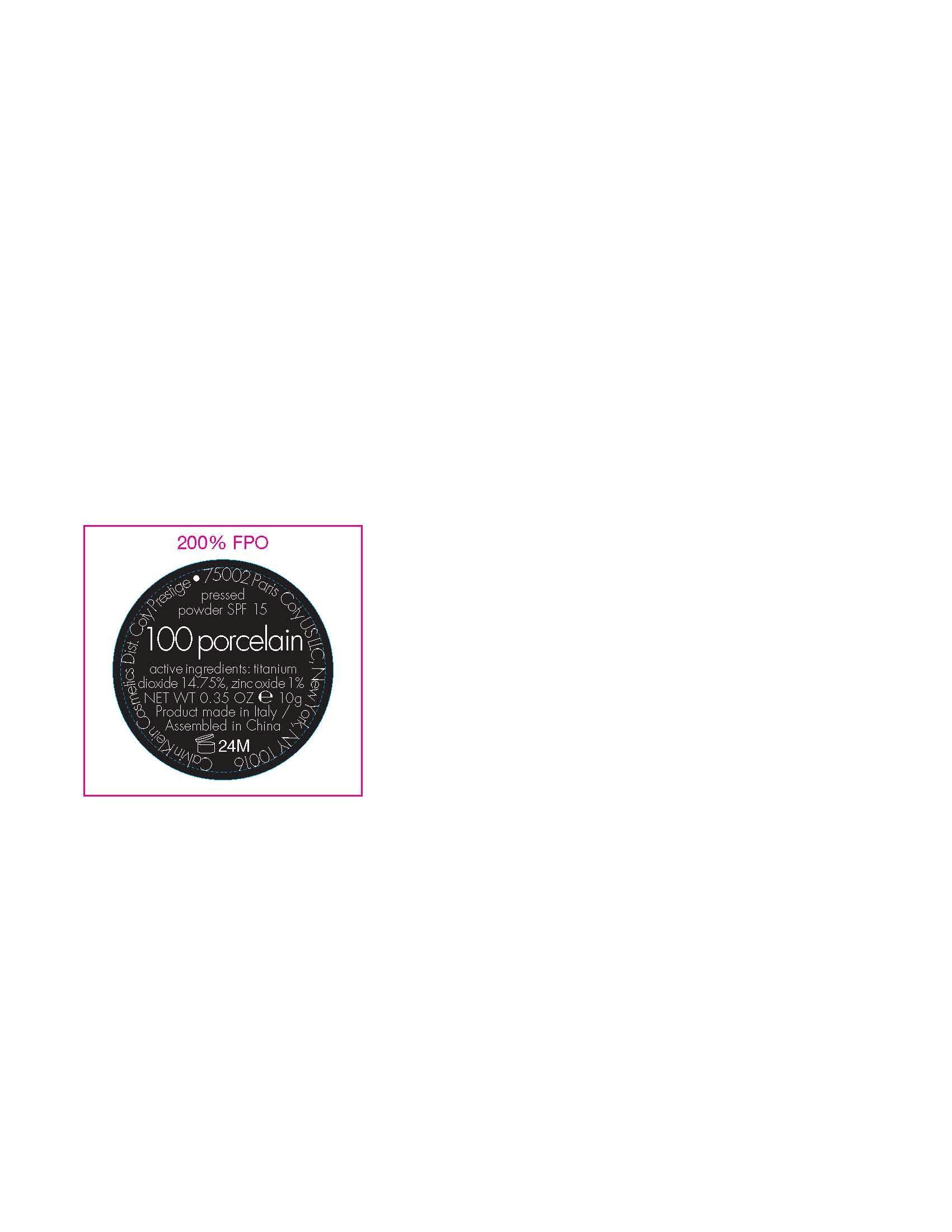 DRUG LABEL: ck one airlight pressed powder spf 15
NDC: 66184-490 | Form: POWDER
Manufacturer: Coty US LLC
Category: otc | Type: HUMAN OTC DRUG LABEL
Date: 20131119

ACTIVE INGREDIENTS: Titanium Dioxide  1.475 mg/10 g; Zinc Oxide 100 mg/10 g
INACTIVE INGREDIENTS: Talc ; Dimethicone ; Zinc Stearate ; Silicon Dioxide; Phenyl Trimethicone ; Starch, corn; Phenoxyethanol ; Hexylene Glycol  ; Mica 

Active Ingredients

ACTIVE INGREDIENT

Titanium Dioxide 14.75%

Zinc Oxide 1%

INACTIVE INGREDIENT

Talc, Dimethicone, Polymethylsilsequioxane, Dimethicone/Vinyl Dimethicone Crosspolymer, Zinc Stearate, Silica, Phenyl Trimthicone, Synthetic Fluorphlogopite, Caprylyl Methicone, Caprylyl Glycol, Methicone, Zea Mays (Corn) sTarch, Phenoxyethanol, Hyxylene Glycol, [May contain: Iron Oxides, Mica]